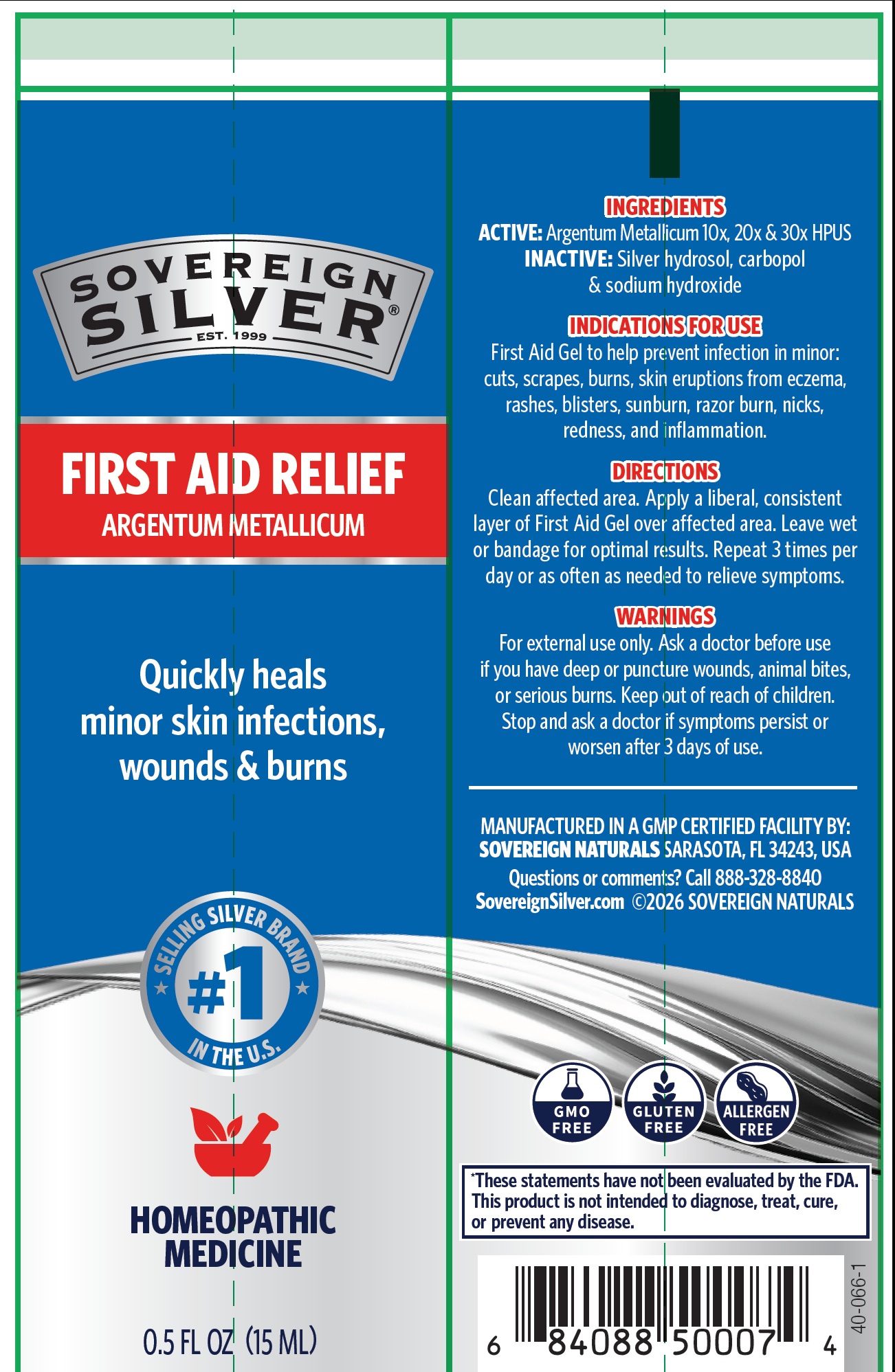 DRUG LABEL: SOVEREIGN SILVER FIRST AID HOMEOPATHIC MEDICINE
NDC: 52166-018 | Form: GEL
Manufacturer: Natural Immunogenics Corp.dba SOVEREIGN NATURALS
Category: homeopathic | Type: HUMAN OTC DRUG LABEL
Date: 20251124

ACTIVE INGREDIENTS: SILVER 30 [hp_X]/1 mL
INACTIVE INGREDIENTS: CARBOMER HOMOPOLYMER, UNSPECIFIED TYPE; CARBOMER HOMOPOLYMER TYPE B (ALLYL PENTAERYTHRITOL CROSSLINKED); SODIUM HYDROXIDE

ACTIVE INGREDIENT

Ingredients

ACTIVE: ARGENTUM METALLICUM 10X, 20X, 30X HPUS

Purpose

TOPICAL HEALING – COMBATS AND QUICKLY HEALS MINOR SKIN INFECTIONS, WOUNDS AND BURNS

Uses

FIRST AID GEL TO HELP PREVENT INFECTION IN MINOR CUTS, SCRAPES, BURNS, SKIN ERUPTIONS FROM ECZEMA, RASHES, BLISTERS, SUNBURN, RAZOR BURN, MINOR NICKS, REDNESS AND MINOR INFLAMMATION

Keep out of reach of children.

Warnings

FOR EXTERNAL USE ONLY.ASK A DOCTOR BEFORE USE IF YOU HAVE DEEP OR PUNCTURE WOUNDS, ANIMAL BITES OR SERIOUS BURNS. KEEP OUT OF REACH OF CHILDREN. STOP AND ASK A DOCTOR IF SYMPTOMS PERSIST OR WORSEN AFTER 3 DAYS OF USE. DO NOT USE IF THE SEAL IS BROKEN.

Directions

CLEAN AFFECTED AREA. APPLY A LIBERAL CONSISTENT LAYER OF FIRST AID GEL OVER AFFECTED AREA. LEAVE WET OR BANDAGE FOR OPTIMAL RESULTS. REPEAT 3 TIMES PER DAY OR AS OFTEN AS NEEDED TO RELIEVE SYMPTOMS. SAFE ON SENSITIVE SKIN.

Inactive Ingredients

CARBOPOL, SILVER HYDROSOL AND SODIUM HYDROXIDE